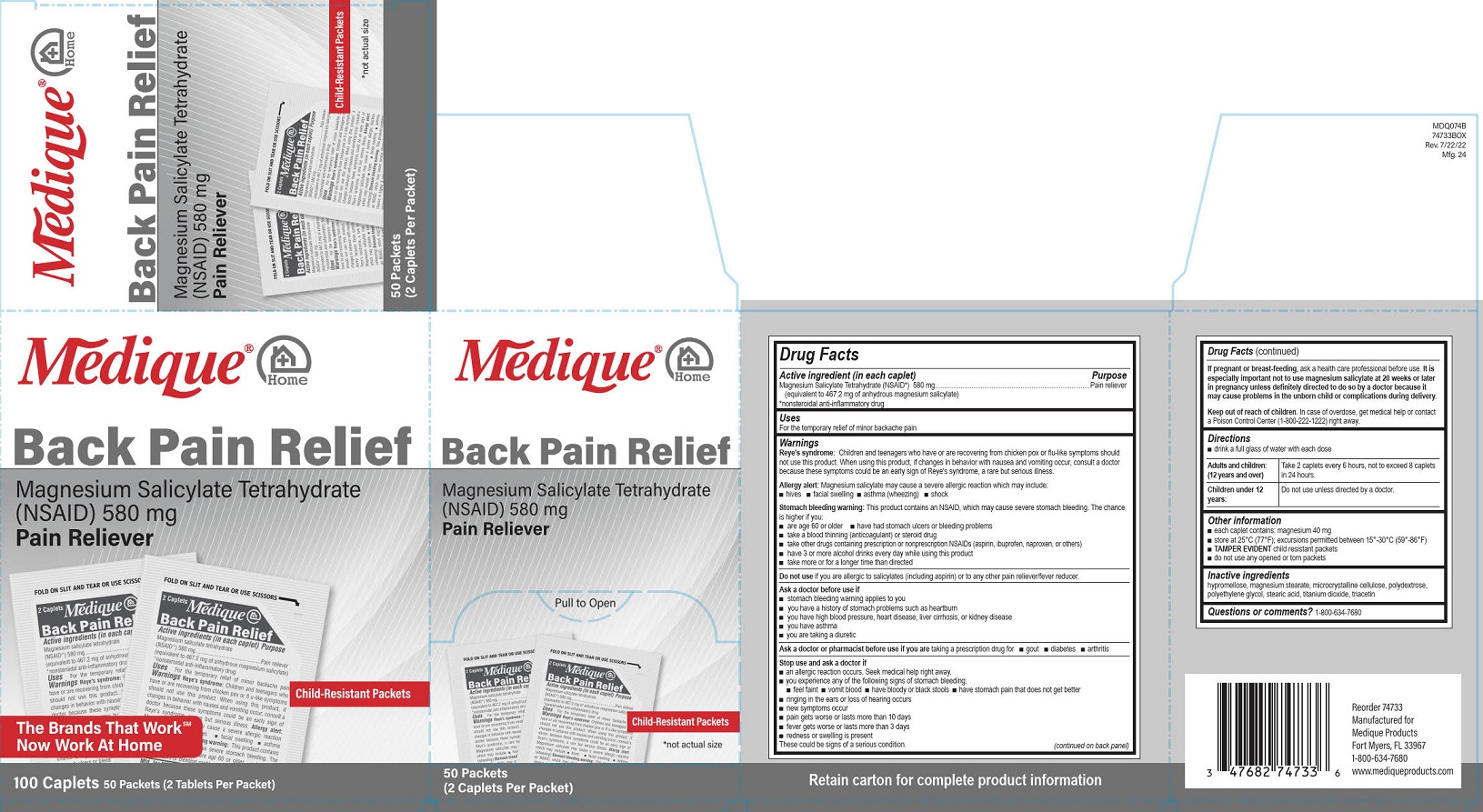 DRUG LABEL: Medique at Home Back Pain Relief
NDC: 47682-747 | Form: TABLET, FILM COATED
Manufacturer: Unifirst First Aid Corporation
Category: otc | Type: HUMAN OTC DRUG LABEL
Date: 20250909

ACTIVE INGREDIENTS: MAGNESIUM SALICYLATE 580 mg/1 1
INACTIVE INGREDIENTS: CELLULOSE, MICROCRYSTALLINE; POLYDEXTROSE; POLYETHYLENE GLYCOL, UNSPECIFIED; TITANIUM DIOXIDE; MAGNESIUM STEARATE; HYPROMELLOSE, UNSPECIFIED; STEARIC ACID; TRIACETIN

Medique @ Home Back Pain Relief

Drug Facts

Active ingredient (in each caplet)

Magnesium Salicylate Tetrahydrate (NSAID)* 580 mg

(equivalent to 467.2 mg of anhydrous magnesium salicylate)

*nonsteroidal anti-inflammatory drug

Purpose

Pain reliever

Uses

For the temporary relief of minor backache pain

Warnings

Reye's syndrome: Children and teenagers who have or are recovering from chicken pox or flu-like symptoms should not use this product. When using this product, if changes in behavior with nausea and vomiting occur, consult a doctor because these symptoms could be an early sign of Reye's syndrome, a rare but serious illness.

Allergy alert:

Magnesium salicylate may cause a severe allergic reaction which may include:

■ hives

■ facial swelling

■ asthma (wheezing)

■ shock

Stomach bleeding warning:

This product contains an NSAID, which may cause severe stomach bleeding. The chance is higher if you

■ are age 60 or older

■ have had stomach ulcers or bleeding problems

■ take a blood thinning (anticoagulant) or steroid drug

■ take other drugs containing prescription or nonprescription NSAIDs (aspirin, ibuprofen, naproxen, or others)

■ have 3 or more alcohol drinks every day while using this product

■ take more or for a longer time than directed

Do not use if you are allergic to salicylates (including aspirin) or to any other pain reliever/fever reducer.

Ask a doctor before use if

■ stomach bleeding warning applies to you

■ you have a history of stomach problems such as heartburn

■ you have high blood pressure, heart disease, liver cirrhosis, or kidney disease

■ you have asthma

■ you are taking a diuretic

Ask a doctor or pharmacist before use if you are taking a prescription drug for

■ gout

■ diabetes

■ arthritis

Stop use and ask a doctor if

■ an allergic reaction occurs. Seek medical help right away.

■ you experience any of the following signs of stomach bleeding: ■ feel faint ■ vomit blood ■ have bloody or black stools ■ have stomach pain that does not get better

■ if ringing in the ears or loss of hearing occurs

■ new symptoms occur

■ pain gets worse or lasts more than 10 days

■ fever gets worse or lasts more than 3 days

■ redness or swelling is present

These could be signs of a serious condition.

PREGNANCY OR BREAST FEEDING

If pregnant or breast-feeding, ask a health professional before use. It is especially important not to use magnesium salicylate at 20 weeks or later in pregnancy unless definitely directed to do so by a doctor because it may cause problems in the unborn child or complications during delivery.

Keep out of reach of children. In case of overdose, get medical help or contact a Poison Control Center
(1-800-222-1222) right away.

Directions

■ drink a full glass of water with each dose

Adults and children: (12 years and over) Take 2 caplets every 6 hours, not to exceed 8 caplets in 24 hours

Children under 12 years: Do not use unless directed by a doctor

Other information

■ each caplet contains: magnesium 40 mg

■ store at 25°C (77°F); excursions permitted between 15°-30°C (59°-86°F)

■ TAMPER EVIDENT child resistant packets

■ do not use any opened or torn packets

Inactive ingredients

hypromellose, magnesium stearate, microcrystalline cellulose, polydextrose, polyethylene glycol, stearic acid, titanium dioxide, triacetin

Questions or comments? 1-800-634-7680

PACKAGE LABEL

Medique® @ Home

Back Pain Relief

Magnesium Salicylate Tetrahydrate

(NSAID) 580 mg

Pain Reliever

Pull to Open

Child-Resistant Packets

*not actual size

50 Packets

(2 Caplets Per Packet)